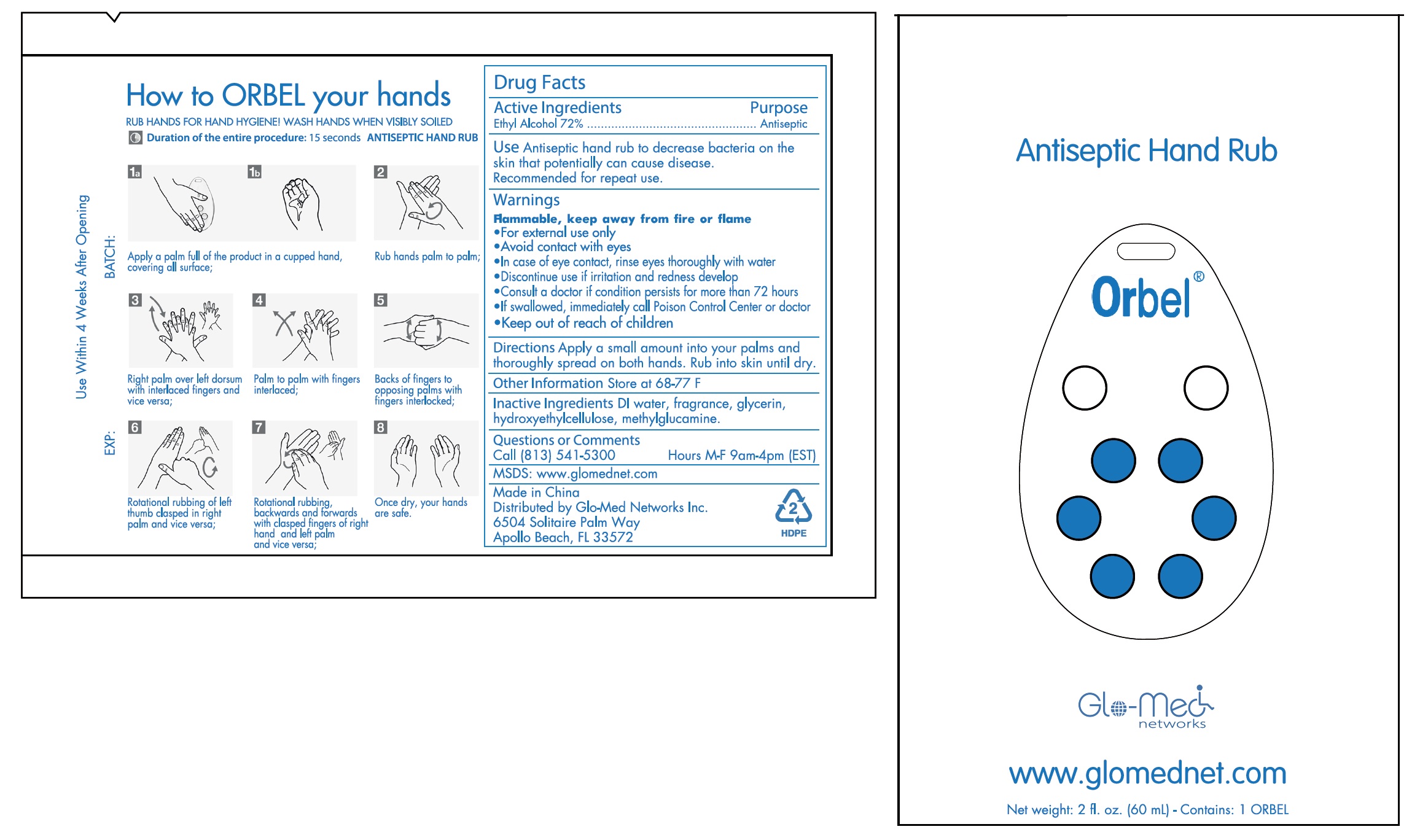 DRUG LABEL: Orbel Antiseptic Hand Rub
NDC: 79723-001 | Form: GEL
Manufacturer: Glo-Med Networks Inc.
Category: otc | Type: HUMAN OTC DRUG LABEL
Date: 20200925

ACTIVE INGREDIENTS: ALCOHOL 0.72 mL/1 mL
INACTIVE INGREDIENTS: WATER; GLYCERIN; HYDROXYETHYL CELLULOSE, UNSPECIFIED; MEGLUMINE

Orbel Antiseptic Hand Rub

Active Ingredients

Ethyl Alcohol 72%

Purpose

Antiseptic

Use

Antiseptic hand rub to decrease bacteria on the skin that potentially can cause disease. Recommended for repeated use.

Warnings

Flammable, keep away from fire or flame

- For external use only
- Avoid contact with eyes
- In case of eye contact, rinse eyes thoroughly with water
- Discontinue use if irritation and redness develop
- consult a doctor if condition persists for more than 72 hours
- If swallowed, immediately call Poison Control Center or doctor

Directions

Apply a small amount into your palms and thoroughly spread on both hands. Rub into skin until dry.

Other Information

Store at 68-77F

Inactive Ingredients

DI water, fragrance, glycerin, hydroxyethylcellulose, methylglucamine.

Questions or Comments

Call [813] 541-5300

Hours M-F 9am-4pm (EST)